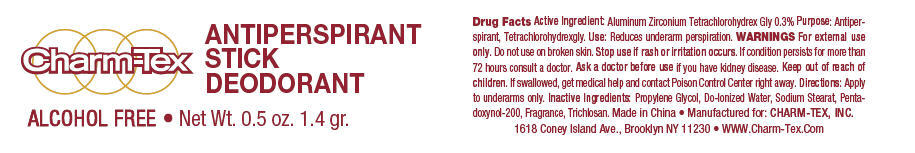 DRUG LABEL: Charm-Tex 
NDC: 40057-4000 | Form: STICK
Manufacturer: Charm-Tex, Inc
Category: otc | Type: HUMAN OTC DRUG LABEL
Date: 20120301

ACTIVE INGREDIENTS: ALUMINUM ZIRCONIUM TETRACHLOROHYDREX GLY 7.8 g/100 g
INACTIVE INGREDIENTS: PROPYLENE GLYCOL; WATER; SODIUM STEARATE; TRICLOSAN

Charm-Tex Stick Deodorant

Drug Facts

Active Ingredient

Aluminum Zirconium Tetrachlorohydrex Gly 0.3%

Purpose

Antiperspirant, Tetrachlorohydrexgly.

Use

Reduces underarm perspiration.

WARNINGS

For external use only.

Do not use on broken skin.

Stop use if rash or irritation occurs. If condition persists for more than 72 hours consult a doctor.

Ask a doctor before use if you have kidney disease.

Keep out of reach of children. If swallowed, get medical help and contact Poison Control Center right away.

Directions

Apply to underarms only.

Inactive Ingredients

Propylene Glycol, Do-Ionized Water, Sodium Stearat, Pentadoxynol-200, Fragrance, Trichlosan

Manufactured for: CHARM-TEX, INC.
1618 Coney Island Ave., Brooklyn NY 11230

PRINCIPAL DISPLAY PANEL - 1.4 gr. Applicator Label

Charm-Tex

ANTIPERSPIRANT
STICK
DEODORANT

ALCOHOL FREE
Net Wt. 0.5 oz. 1.4 gr.